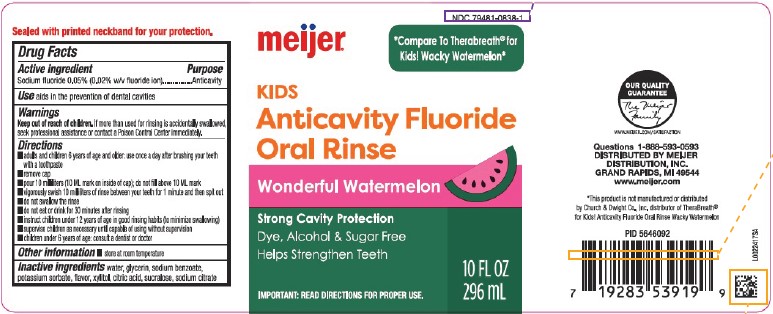 DRUG LABEL: Anticavity fluoride rinse
NDC: 79481-0838 | Form: MOUTHWASH
Manufacturer: Meijer, Inc.
Category: otc | Type: HUMAN OTC DRUG LABEL
Date: 20260219

ACTIVE INGREDIENTS: SODIUM FLUORIDE 0.2 mg/1 mL
INACTIVE INGREDIENTS: GLYCERIN; SODIUM BENZOATE; WATER; POTASSIUM SORBATE; XYLITOL; CITRIC ACID MONOHYDRATE; SUCRALOSE; SODIUM CITRATE, UNSPECIFIED FORM

Meijer 838.000/838AB
Kids Anticavity Fluoride Oral Rinse {Wonderful Watermelon}

TAMPER EVIDENT STATEMENT

SEALED WITH PRINTED NECKBAND FOR YOUR PROTECTION

Active ingredient

Sodium fluoride 0.05% (0.02% w/v fluoride ion)

Purpose

Anticavity

Use

aids in the prevention of dental cavities

Warnings

For this product

Keep out of reach of children.

If more than used for rinsing is accidentally swallowed, seek professional assistance or contact a Poison Control Center immediately.

Directions

- adults and children 6 years of age and older: use once a day after brushing your teeth with a toothpaste
- remove cap
- pour 10 milliliters (10 ML mark on inside of cap); do not fill above 10 ML mark
- vigorously swish 10 milliliters of rinse between your teeth for 1 minute and then spit out
- do not swallow the rinse
- do not eat or drink for 30 minutes after rinsing
- instruct children under 12 years of age in good rinsing habits (to minimize swallowing)
- supervise children as necessary until capable of using without supervision
- children under 6 years of age: consult a dentist or doctor

Other information

- store at room temperature

Inactive ingredients

water, glycerin, sodium benzoate, potassium sorbate, flavor, xylitol, citric acid, sucralose, sodium citrate

ADVERSE REACTIONS

OUR QUALITY GUARANTEE

The Meijer Family

www.meijer.com/satisfaction

Questions 1-888-593-0593

DISTRIBUTED BY MEIJER DISTRIBUTION, INC.

GRAND RAPIDS, MI 49544

www.meijer.com

Disclaimer

*This product is not manufactured or distributed by Church & Dwight Co. Inc., distributor of TheraBreath® for Kids! Anticavity Fluoride Oral Rinse Wacky Watermelon.

PRINCIPAL DISPLAY PANEL

NDC 79481-0838-1

meijer®

COMPARE TO THERABREATH® FOR KIDS! WACKY WATERMELON*

Kids

Anticavity Fluoride

Oral Rinse

Wonderful Watermelon

Strong Cavity Protection

Dye, Alcohol & Sugar Free

Helps Strengthen Teeth

IMPORTANT: read directions for proper use.

10 FL OZ (296 mL)